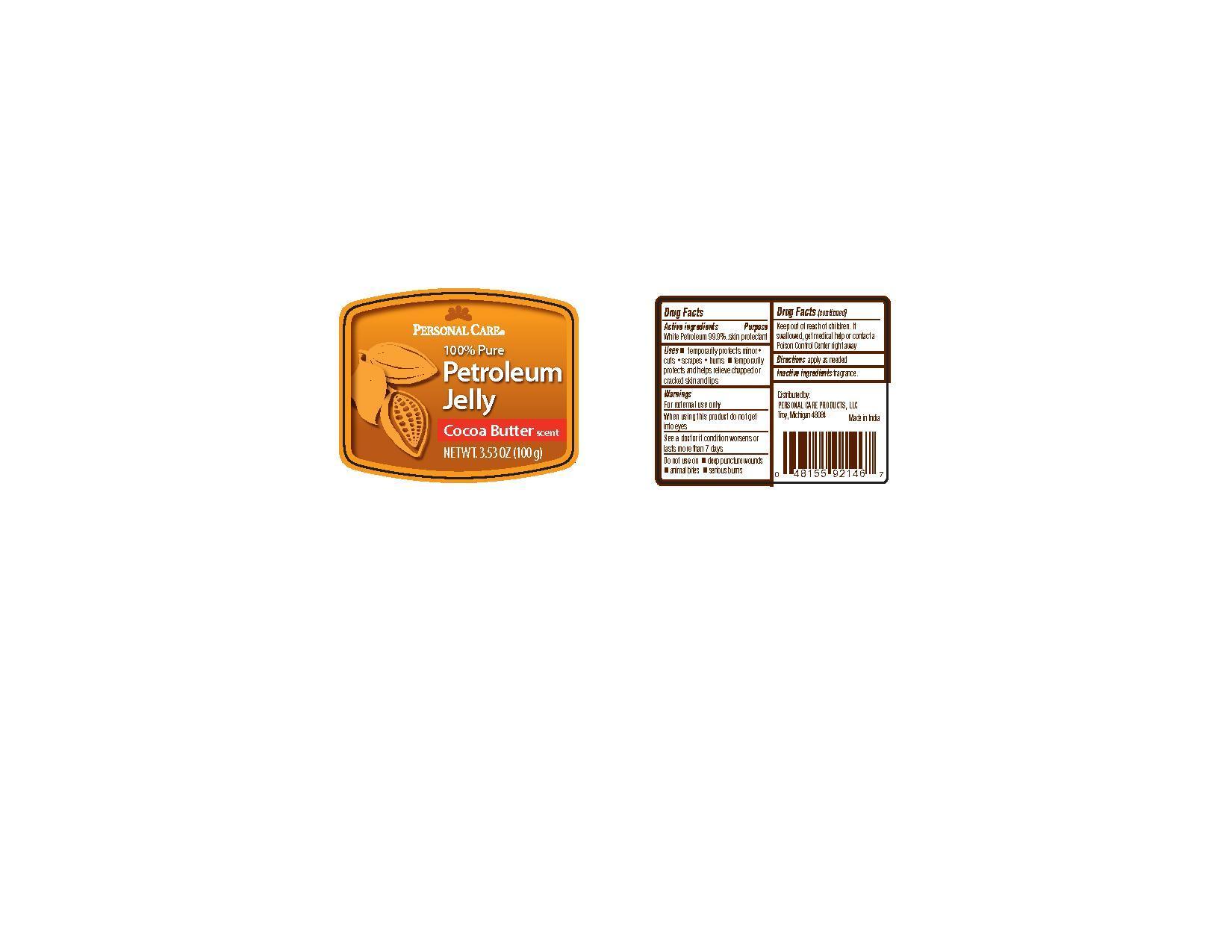 DRUG LABEL: Personal Care Petroleum
NDC: 29500-8050 | Form: JELLY
Manufacturer: PERSONAL CARE PRODUCTS
Category: otc | Type: HUMAN OTC DRUG LABEL
Date: 20120930

ACTIVE INGREDIENTS: PETROLATUM 100 g/100 g

Personal Care 100% Pure Petroleum

Active Ingredients
White Petroleum 99.9%

Purpose

skin protectant

Keep out of reach of children. If swallowed get medical help or contact a Poison Control Center right away.

Uses

Temporarily protects minor cuts, scrapes, burns

Temporarily protects and helps relive chapped or cracked skin and lips

Warnings

For external use only

When using this product do not get into eyes

See a doctor if condition worsens or lasts more than 7 days

Do not use on deep puncture wounds, animal bikes, serious burns

Directions

apply as needed

Inactive Ingredients

Fragrance

PACKAGE LABEL

Personal Care

100% Pure

Petroleum Jelly

Cocoa Butter scent

Net Wt. 3.55 oz (100 g)

Distributed by:

Personal Care Products LLC

Troy Michigan 48084

Made in India